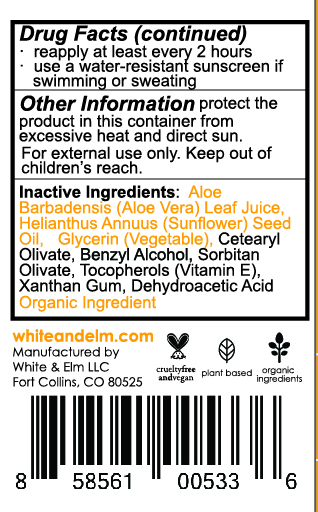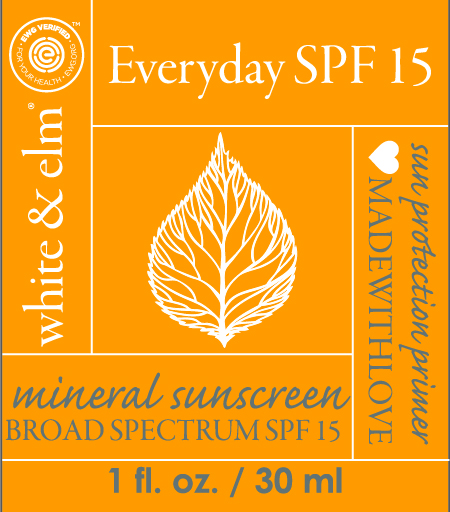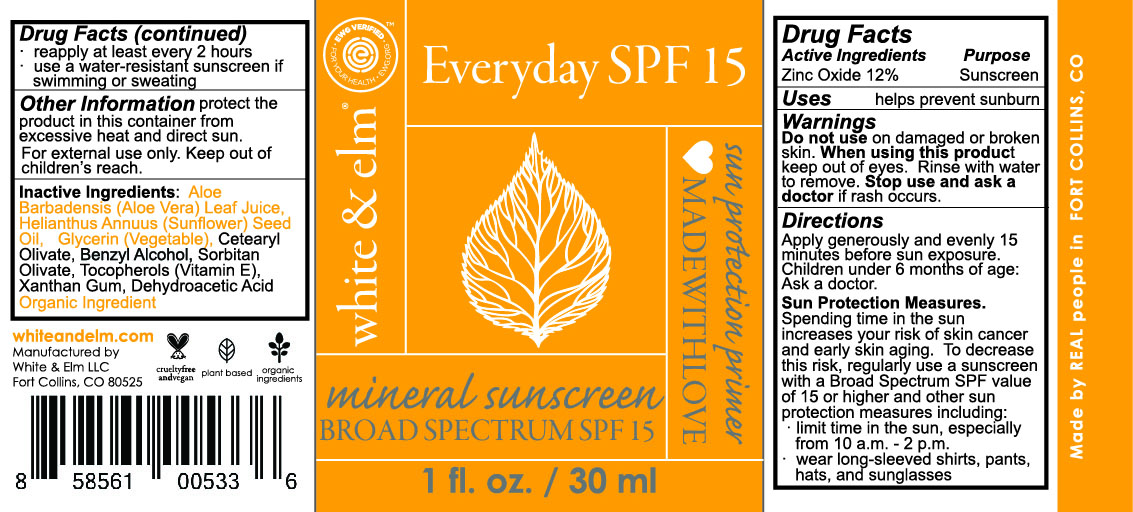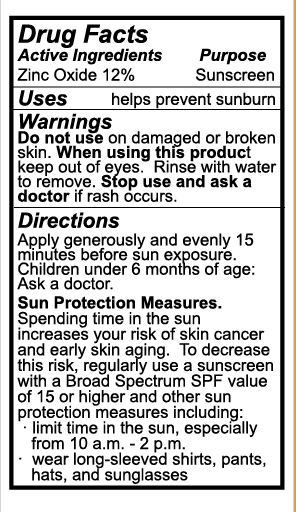 DRUG LABEL: White and Elm Everyday SPF 15
NDC: 70840-001 | Form: LOTION
Manufacturer: White & Elm LLC
Category: otc | Type: HUMAN OTC DRUG LABEL
Date: 20170206

ACTIVE INGREDIENTS: ZINC OXIDE 146 mg/1 mL
INACTIVE INGREDIENTS: SUNFLOWER OIL; ALOE; CETEARYL OLIVATE; BENZYL ALCOHOL; TOCOPHEROL; XANTHAN GUM; GLYCERIN; SORBITAN OLIVATE; DEHYDROACETIC ACID

Active Ingredient Listing

Active Ingredients: Zinc Oxide12%. Purpose: Sunscreen

ASK DOCTOR

Children under 6 months of age: Ask a doctor.

INACTIVE INGREDIENT

Inactive Ingredients: Aloe Barbadensis (Aloe Vera) Leaf Juice, Helianthus Annuus (Sunflower) Seed Oil, Glycerin (Vegetable), Cetearyl Olivate, Benzyl Alcohol, Sorbitan Olivate, Tocopherols (Vitamin E), Xanthan Gum, Dehydroacetic Acid

Do not use on damaged or broken skin. When using this product keep out of eyes. Rinse with water to remove. Stop use and ask a doctor if rash occurs.

Do not use on damaged or broken skin.

Keep out of children’s reach.

PACKAGE LABEL

Mineral Sunscreen

Broad Spectrum SPF 15